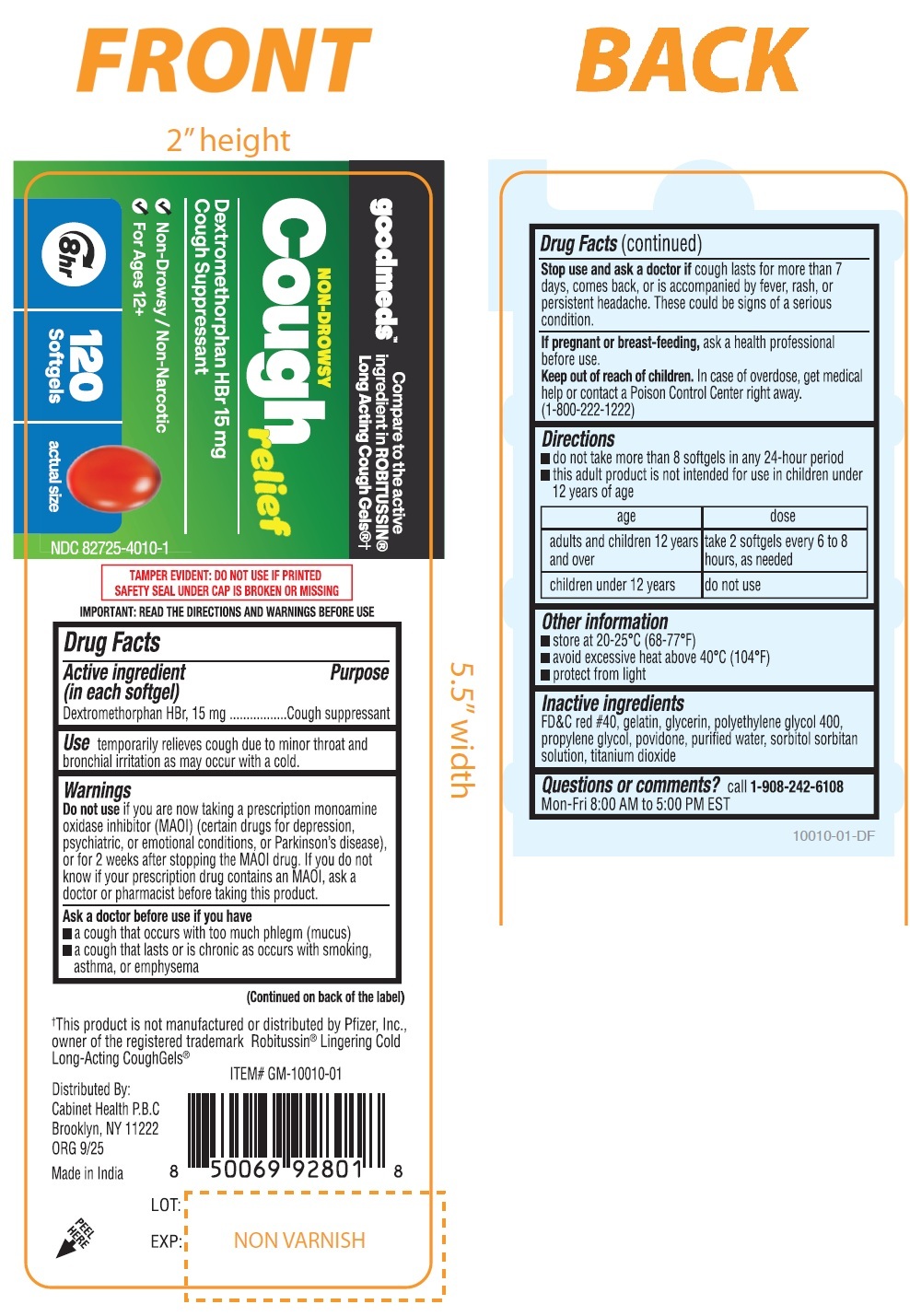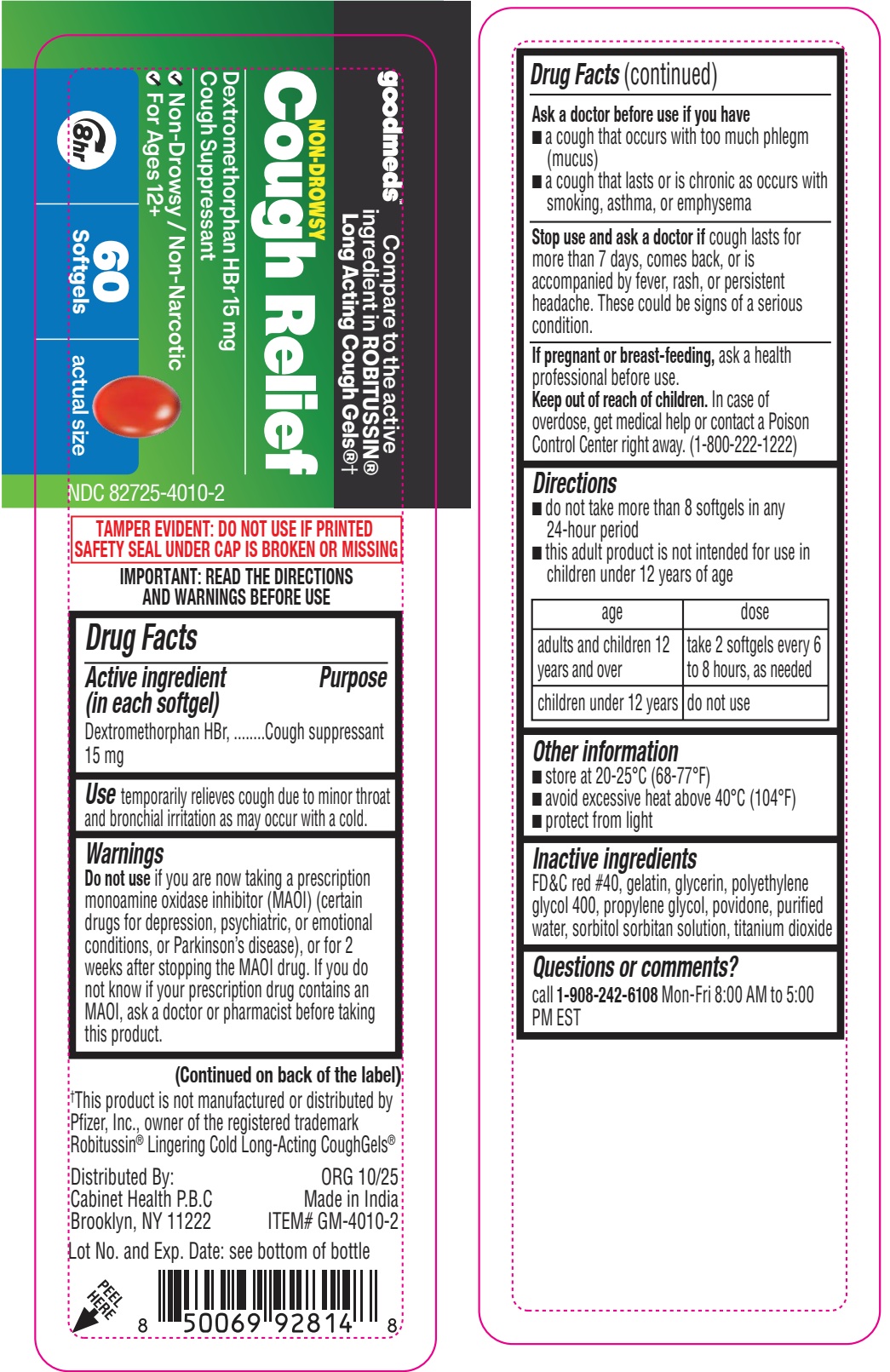 DRUG LABEL: Goodmeds Non-Drowsy Cough Relief
NDC: 82725-4010 | Form: CAPSULE, LIQUID FILLED
Manufacturer: Cabinet Health P.B.C.
Category: otc | Type: HUMAN OTC DRUG LABEL
Date: 20251229

ACTIVE INGREDIENTS: DEXTROMETHORPHAN HYDROBROMIDE 15 mg/1 1
INACTIVE INGREDIENTS: FD&C RED NO. 40; GELATIN; GLYCERIN; POLYETHYLENE GLYCOL 400; PROPYLENE GLYCOL; POVIDONE; WATER; SORBITOL; SORBITAN; TITANIUM DIOXIDE

Goodmeds Non-Drowsy Cough Relief

Active ingredient (in each softgel)

Dextromethorphan HBr, 15 mg

Purpose

Cough suppressant

Uses

temporarily relieves cough due to minor throat and bronchial irritation as may occur with a cold.

Warnings

Do not use

if you are now taking a prescription monoamine oxidase inhibitor (MAOI) (cenain drugs for depression, psychiatric, cr emotional conditions, or Parkinson's disease), cr for 2 weeks after stopping the MAOI drug. If you do not know if your prescription drug contains an MAOI, ask a doctor or pharmacist before taking this product.

Ask a doctor before use if you have

• a cough that occurs with too much phlegm (mucus)
• a cough that lasts or is chronic as occurs with smoking, asthma, or emphysema

Stop use and ask a doctor if

cough lasts for more than 7 days, comes back, or is accompanied by fever, rash, or persistent headache. These could be signs of a serious condition.

If pregnant or breast-feeding,

ask a health professional before use.

Keep out of reach of children.

In case of overdose, get medical help or contact a Poison Control Center right away. (1-800-222-1222)

Directions

do not take more than 8 softgels in any 24-hour period
this adult product is not intended for use in children under 12 years of age

age | dose
adults and children 12 years and over | take 2 softgels every 6 to 8 hours, as needed
children under 12 years | do not use

Other information

• store at 20-25ºC (68-77ºF)
• avoid excessive heat above 40ºC (104ºF)
• protect from light

Inactive ingredients

FD&C red #40, gelatin, glycerin, polyethylene glycol 400, propylene glycol, povidone, purified water, sorbitol sorbitan solution. titanium dioxide

Questions or Comments?

call 1-908-242-6108 Mon-Fri 8:00 AM to 5:00 PM EST